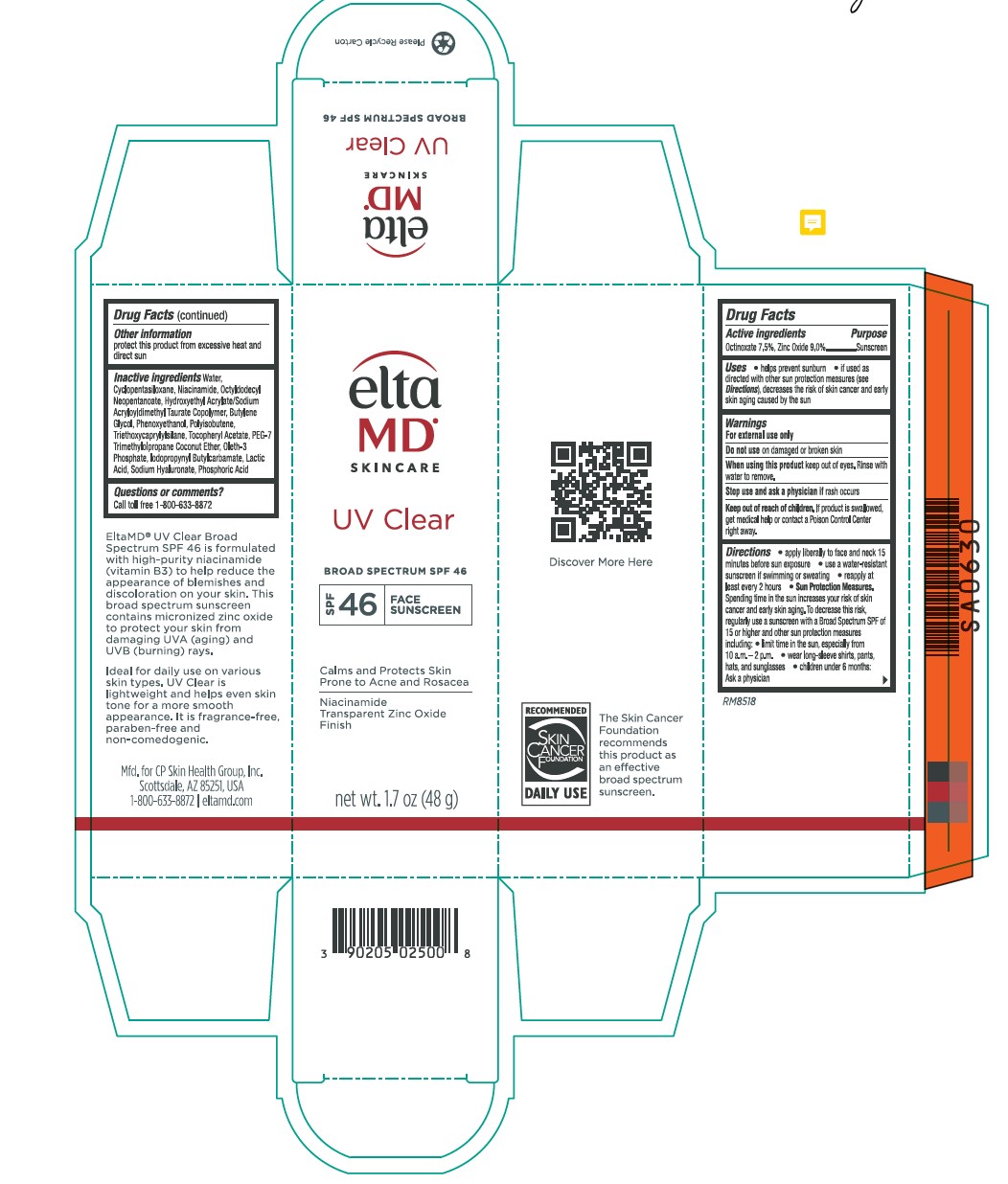 DRUG LABEL: EltaMD UV Clear SPF46
NDC: 72043-2500 | Form: LOTION
Manufacturer: CP Skin Health Group, Inc.
Category: otc | Type: HUMAN OTC DRUG LABEL
Date: 20250604

ACTIVE INGREDIENTS: ZINC OXIDE 90 g/1000 g; OCTINOXATE 75 g/1000 g
INACTIVE INGREDIENTS: BUTYLENE GLYCOL; IODOPROPYNYL BUTYLCARBAMATE; PHENOXYETHANOL; WATER; LACTIC ACID; HYALURONATE SODIUM; NIACINAMIDE; CYCLOMETHICONE 5; .ALPHA.-TOCOPHEROL ACETATE, DL-; OCTYLDODECYL BENZOATE; OLETH-3 PHOSPHATE; TRIETHOXYCAPRYLYLSILANE; HYDROXYETHYL ACRYLATE/SODIUM ACRYLOYLDIMETHYL TAURATE COPOLYMER (100000 MPA.S AT 1.5%); POLYISOBUTYLENE (1000 MW)

EltaMD UV Clear SPF46

Warnings

For external use only Do not use on damaged or broken skin When using the product keep out of eyes. Rinse with water to remove Stop use and ask a physician if rash occurs Keep out of reach of children. If product is swallowed, get medical help or contact a Poison Control Center right away.

Active Ingredients

Zinc Oxide 9.0% Sunscreen

Octinoxate 7.5% Sunscreen

Uses

Helps Prevent Sunburn If used as directed with other sun protection measures (See Directions), decreases the risk of skin cancer and early skin aging caused by the sun.

Uses

Helps Prevent Sunburn If used as directed with other sun protection measures (See Directions), decreases the risk of skin cancer and early skin aging caused by the sun.

Directions

apply liberally to face and neck 15 minutes before sun exposure use a water-resistant sunscreen if swimming or sweating reapply at least every 2 hours Sun Protection Measures. Spending time in the sun increases your risk of skin cancer and early skin aging. To decrease this risk, regularly use a sunscreen with a broad-spectrum SPF of 15 or higher and other sun protection measures including: limit time in the sun, especially from 10 a.m.- 2 p.m. wear long-sleeve shirts, pants, hats and sunglasses children under 6 months: Ask a physician

Inactive Ingredients

Purified water, Cyclopentasiloxane, Niacinamide, Octyldodecyl Neopentanoate, Hydroxyethyl Acrylate/Sodium Acryloyldimethyl Taurate Copolymer, Polyisobutene, PEG-7 Trimethylolpropane Coconut Ether, Sodium Hyaluronate, Tocopheryl Acetate, Lactic Acid, Oleth-3 Phosphate, Phenoxyethanol, Butylene Glycol, Iodopropynyl Butylcarbamate, Triethoxycaprylylsilane

KEEP OUT OF REACH OF CHILDREN